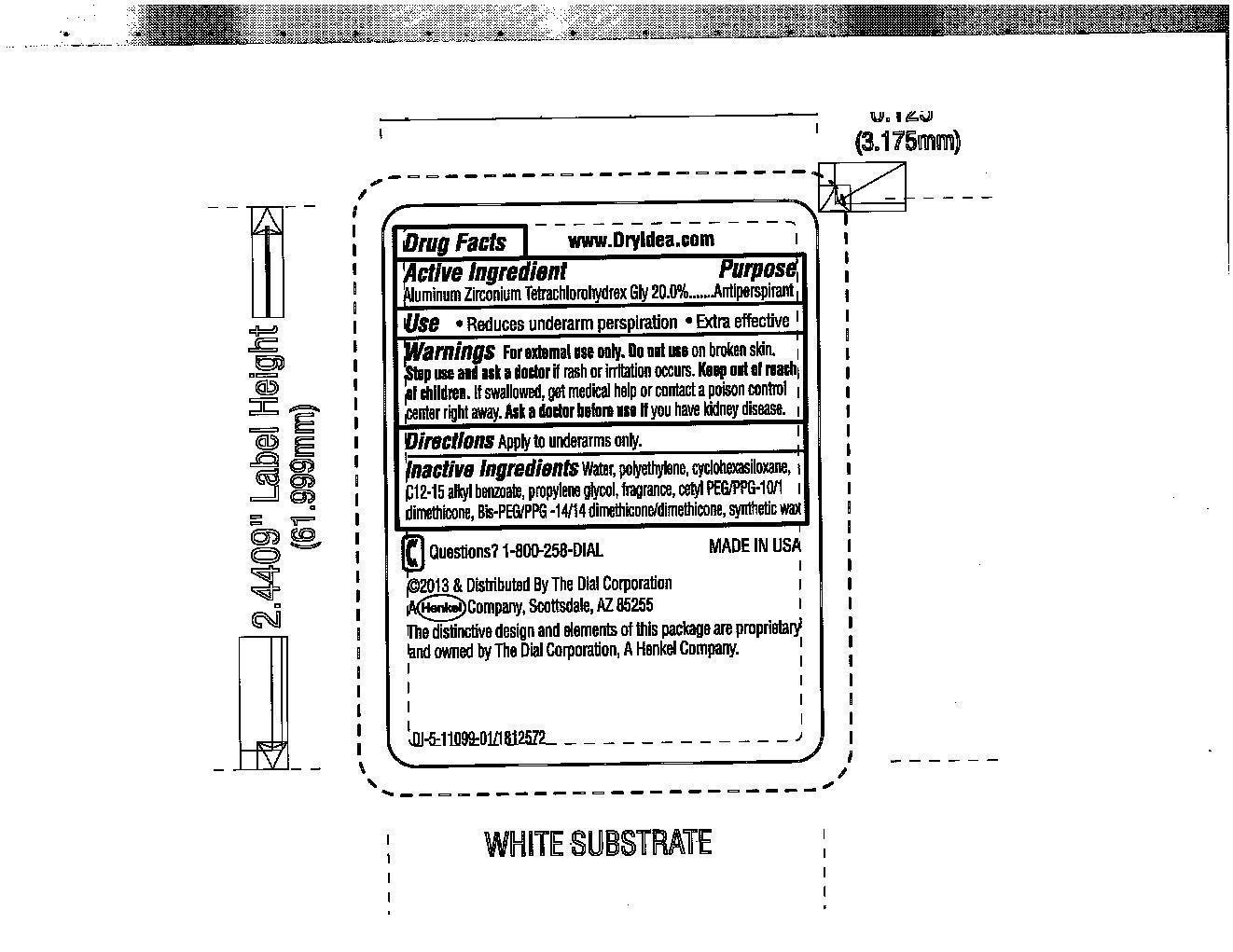 DRUG LABEL: Dry Idea Clinical Clear
NDC: 51815-223 | Form: STICK
Manufacturer: VVF Illinois Services
Category: otc | Type: HUMAN OTC DRUG LABEL
Date: 20140402

ACTIVE INGREDIENTS: ALUMINUM ZIRCONIUM TETRACHLOROHYDREX GLY 9.6 g/48 g
INACTIVE INGREDIENTS: WATER; HIGH DENSITY POLYETHYLENE; DODECAMETHYLPENTASILOXANE; C12-15 ALKYL BENZOATE; PROPYLENE GLYCOL; CETYL PEG/PPG-10/1 DIMETHICONE (HLB 2); PEG/PPG-14/4 DIMETHICONE; SYNTHETIC WAX (1200 MW)

Dry Idea Clinical Clear Clean

Active Ingredient

Aluminum Zirconium Tetrachlorohydrex GLY 20.0%

Purpose

Antiperspirant

Warnings

For external use only. Do not use on broken skin.

Stop use and ask a doctor if rash or irritation occurs.

Keep out of reach of children

If swallowed get medical help or contact a poison control center right away.

Ask a doctor before use if you have kidney disease.

Use

Reduces underarm perspiration Extra Effective

INACTIVE INGREDIENT

Water, polyethylene, cyclohexasiloxane, C12-15 alkyl benzoate, proylene glycol, fragrance, cetyl PEG/PPG-10-1 dimethicone, Bis-PEG/PPG-14/14 dimethicone/dimethicone, synthetic wax

DOSAGE AND ADMINISTRATION

Apply to underarms only.

Questions?

1-800-258-DIAL